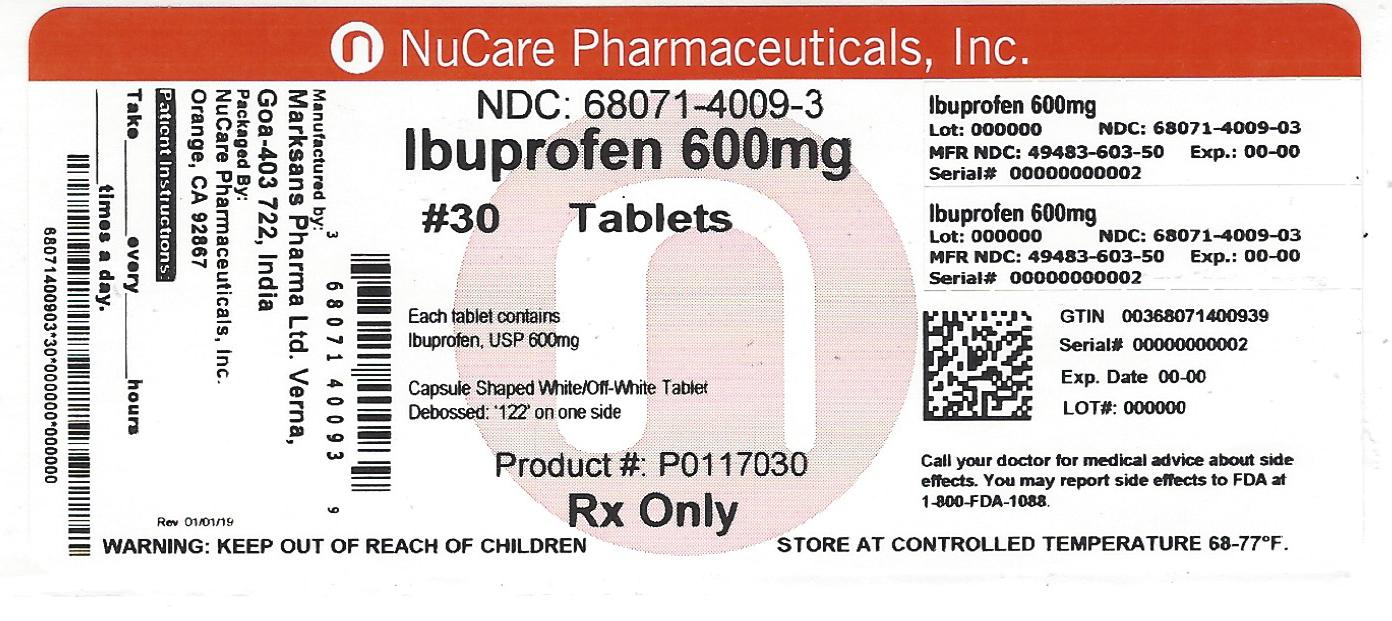 DRUG LABEL: IBUPROFEN
NDC: 68071-4009 | Form: TABLET, FILM COATED
Manufacturer: NuCare Pharmaceuticals,Inc.
Category: prescription | Type: HUMAN PRESCRIPTION DRUG LABEL
Date: 20240717

ACTIVE INGREDIENTS: IBUPROFEN 600 mg/1 1
INACTIVE INGREDIENTS: SILICON DIOXIDE; CROSCARMELLOSE SODIUM; MAGNESIUM STEARATE; CELLULOSE, MICROCRYSTALLINE; POLYETHYLENE GLYCOL, UNSPECIFIED; POLYVINYL ALCOHOL; STARCH, PREGELATINIZED CORN; TALC; TITANIUM DIOXIDE

HOW SUPPLIED

NDC 68071-4009-7 Bottles of 15

NDC 68071-4009-2 Botles of 20

NDC 68071-4009-1 Bottles of 21

NDC 68071-4009-3 Bottles of 30

NDC 68071-4009-4 Bottles of 40

NDC 68071-4009-5 Bottles of 50

NDC 68071-4009-6 Bottles of 60

NDC 68071-4009-9 Bottles of 90